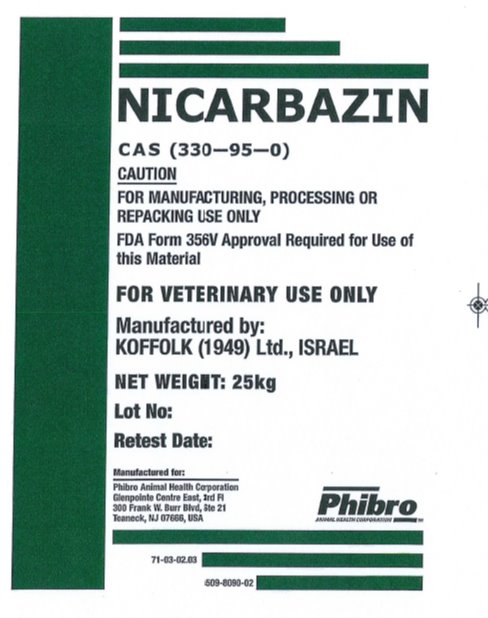 DRUG LABEL: Nicarbazin
NDC: 54277-4988 | Form: POWDER
Manufacturer: Phibro Animal Health Ltd
Category: other | Type: BULK INGREDIENT - ANIMAL DRUG
Date: 20231120

ACTIVE INGREDIENTS: NICARBAZIN 1 kg/1 kg

Nicarbazin

CAS (330-95-0)

CAUTION:

For Manufacturing , Processing or Repackaging Use Only

FDA Form 356v Approval Required for Use of this Material

FOR VETERINARY USE ONLY

Manufactured by:

Phibro Animal Health Ltd,. Israel

Net Weight: 25 KG

Manufactured for:

Phibro Animal Health Corporation

GlenPointe Centre East, 3rd Floor

300 Frank W. Burr Blvd, Ste 21

Teaneck , NJ 07666, USA

Nicarbazin Label